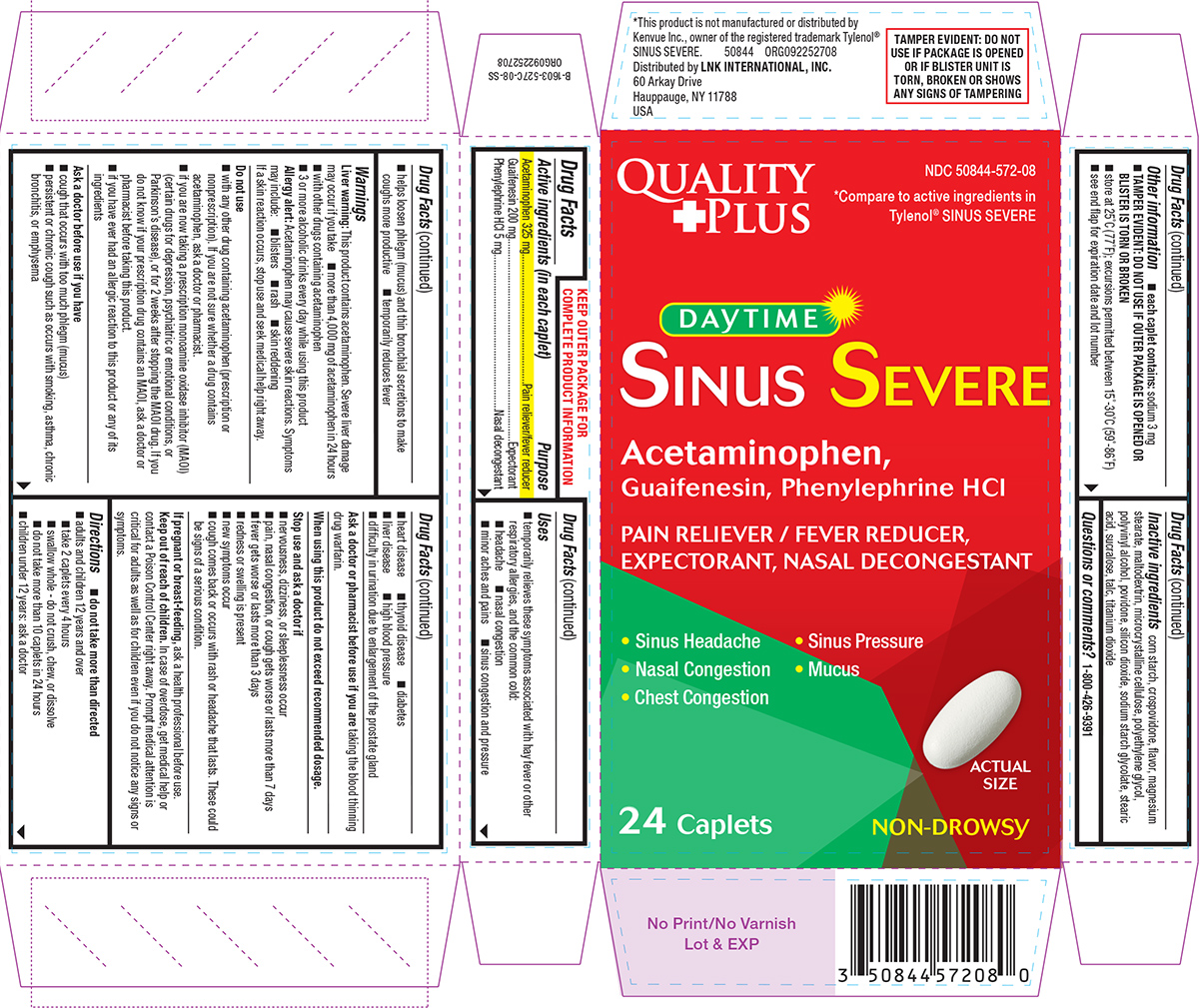 DRUG LABEL: Sinus Severe
NDC: 50844-572 | Form: TABLET, FILM COATED
Manufacturer: L.N.K. International, Inc.
Category: otc | Type: HUMAN OTC DRUG LABEL
Date: 20260209

ACTIVE INGREDIENTS: ACETAMINOPHEN 325 mg/1 1; GUAIFENESIN 200 mg/1 1; PHENYLEPHRINE HYDROCHLORIDE 5 mg/1 1
INACTIVE INGREDIENTS: STARCH, CORN; CROSPOVIDONE, UNSPECIFIED; MAGNESIUM STEARATE; MALTODEXTRIN; MICROCRYSTALLINE CELLULOSE; POLYETHYLENE GLYCOL, UNSPECIFIED; POLYVINYL ALCOHOL, UNSPECIFIED; POVIDONE, UNSPECIFIED; SILICON DIOXIDE; SODIUM STARCH GLYCOLATE TYPE A POTATO; STEARIC ACID; SUCRALOSE; TALC; TITANIUM DIOXIDE

Quality Plus 44-527C

Active ingredients (in each caplet)

Acetaminophen 325 mg
Guaifenesin 200 mg
Phenylephrine HCl 5 mg

Purpose

Pain reliever/fever reducer
Expectorant
Nasal decongestant

Uses

- temporarily relieves these symptoms associated with hay fever or other respiratory allergies, and the common cold:
  - headache
  - nasal congestion
  - minor aches and pains
  - sinus congestion and pressure
- helps loosen phlegm (mucus) and thin bronchial secretions to make coughs more productive
- temporarily reduces fever

Warnings

Liver warning: This product contains acetaminophen. Severe liver damage may occur if you take

- more than 4,000 mg of acetaminophen in 24 hours
- with other drugs containing acetaminophen
- 3 or more alcoholic drinks every day while using this product

Allergy alert: Acetaminophen may cause severe skin reactions. Symptoms may include:

- blisters
- rash
- skin reddening

If a skin reaction occurs, stop use and seek medical help right away.

Do not use

- with any other drug containing acetaminophen (prescription or nonprescription). If you are not sure whether a drug contains acetaminophen, ask a doctor or pharmacist.
- if you are now taking a prescription monoamine oxidase inhibitor (MAOI) (certain drugs for depression, psychiatric or emotional conditions, or Parkinson’s disease), or for 2 weeks after stopping the MAOI drug. If you do not know if your prescription drug contains an MAOI, ask a doctor or pharmacist before taking this product.
- if you have ever had an allergic reaction to this product or any of its ingredients

Ask a doctor before use if you have

- cough that occurs with too much phlegm (mucus)
- persistent or chronic cough such as occurs with smoking, asthma, chronic bronchitis, or emphysema
- heart disease
- thyroid disease
- diabetes
- liver disease
- high blood pressure
- difficulty in urination due to enlargement of the prostate gland

Ask a doctor or pharmacist before use if you are

taking the blood thinning drug warfarin.

When using this product

do not exceed recommended dosage.

Stop use and ask a doctor if

- nervousness, dizziness, or sleeplessness occur
- pain, nasal congestion, or cough gets worse or lasts more than 7 days
- fever gets worse or lasts more than 3 days
- redness or swelling is present
- new symptoms occur
- cough comes back or occurs with rash or headache that lasts. These could be signs of a serious condition.

If pregnant or breast-feeding,

ask a health professional before use.

Keep out of reach of children.

In case of overdose, get medical help or contact a Poison Control Center right away. Prompt medical attention is critical for adults as well as for children even if you do not notice any signs or symptoms.

Directions

- do not take more than directed
- adults and children 12 years and over
  - take 2 caplets every 4 hours
  - swallow whole - do not crush, chew, or dissolve
  - do not take more than 10 caplets in 24 hours
- children under 12 years: ask a doctor

Other information

- each caplet contains: sodium 3 mg
- TAMPER EVIDENT: DO NOT USE IF OUTER PACKAGE IS OPENED OR BLISTER IS TORN OR BROKEN
- store at 25°C (77°F); excursions permitted between 15°-30°C (59°-86°F)
- see end flap for expiration date and lot number

Inactive ingredients

corn starch, crospovidone, flavor, magnesium stearate, maltodextrin, microcrystalline cellulose, polyethylene glycol, polyvinyl alcohol, povidone, silicon dioxide, sodium starch glycolate, stearic acid, sucralose, talc, titanium dioxide

Questions or comments?

1-800-426-9391

Principal Display Panel

Quality Plus

NDC 50844-572-08

*Compare to active ingredients in
Tylenol® SINUS SEVERE

DAYTIME

SINUS SEVERE
Acetaminophen,
Guaifenesin, Phenylephrine HCl

PAIN RELIEVER / FEVER REDUCER
EXPECTORANT, NASAL DECONGESTANT

•Sinus Headache •Sinus Pressure
•Nasal Congestion •Mucus
•Chest Congestion

24 Caplets

ACTUAL SIZE
NON-DROWSY

*This product is not manufactured or distributed by
Kenvue Inc., owner of the registered trademark Tylenol®
SINUS SEVERE. 50844 ORG092252708

Distributed by
LNK INTERNATIONAL, INC.
60 Arkay Drive, Hauppauge, NY 11788
USA

TAMPER EVIDENT: DO NOT
USE IF PACKAGE IS OPENED
OR IF BLISTER UNIT IS
TORN, BROKEN OR SHOWS
ANY SIGNS OF TAMPERING

Quality Plus 44-527